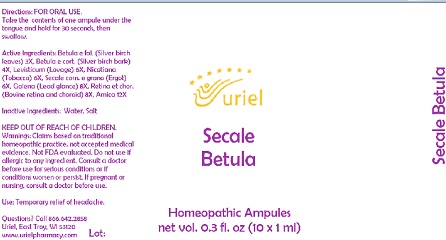 DRUG LABEL: Secale Betula
NDC: 48951-8379 | Form: LIQUID
Manufacturer: Uriel Pharmacy Inc.
Category: homeopathic | Type: HUMAN OTC DRUG LABEL
Date: 20210730

ACTIVE INGREDIENTS: ARNICA MONTANA 12 [hp_X]/1 mL; BETULA PENDULA LEAF 3 [hp_X]/1 mL; CLAVICEPS PURPUREA SCLEROTIUM 6 [hp_X]/1 mL; LEAD SULFIDE 8 [hp_X]/1 mL; BOS TAURUS EYE 8 [hp_X]/1 mL; BETULA PENDULA BARK 4 [hp_X]/1 mL; LEVISTICUM OFFICINALE ROOT 6 [hp_X]/1 mL; TOBACCO LEAF 6 [hp_X]/1 mL
INACTIVE INGREDIENTS: SODIUM CHLORIDE; WATER

Secale Betula

INDICATIONS AND USAGE

Directions: FOR ORAL USE.

DOSAGE AND ADMINISTRATION

Take the contents of one ampule under the tongue and hold for 30 seconds, then swallow.

ACTIVE INGREDIENT

Active Ingredients: Betula e fol. (Silver birch leaves) 3X, Betula e cort. (Silver birch bark) 4X, Levisticum (Lovage) 6X, Nicotiana (Tobacco) 6X, Secale corn. e grano (Ergot) 6X, Galena (Lead glance) 8X, Retina et chor. (Bovine retina and choroid) 8X, Arnica 12X

Inactive Ingredients: Water, Salt

PURPOSE

Use: Temporary relief of headache.

KEEP OUT OF REACH OF CHILDREN.

WARNINGS

Warnings: Claims based on traditional homeopathic practice, not accepted medical evidence. Not FDA evaluated. Do not use if allergic to any ingredient. Consult a doctor before use for serious conditions or if conditions worsen or persist. If pregnant or nursing, consult a doctor before use.

Questions? Call 866.642.2858
Uriel, East Troy, WI 53120
www.urielpharmacy.com Lot: